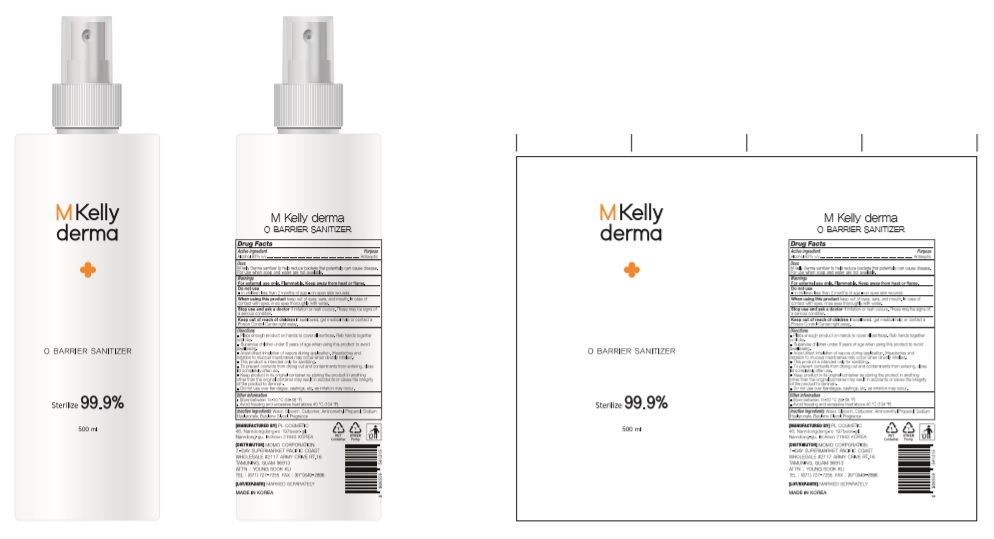 DRUG LABEL: M KELLY DERMA O BARRIER SANITIZER
NDC: 74339-6250 | Form: SPRAY
Manufacturer: PL COSMETIC
Category: otc | Type: HUMAN OTC DRUG LABEL
Date: 20200429

ACTIVE INGREDIENTS: ALCOHOL 310 mL/500 mL
INACTIVE INGREDIENTS: GLYCERIN; CARBOMER HOMOPOLYMER, UNSPECIFIED TYPE; WATER; BUTYLENE GLYCOL; HYALURONATE SODIUM; TROLAMINE

M KELLY DERMA O BARRIER SANITIZER: 74339-6250